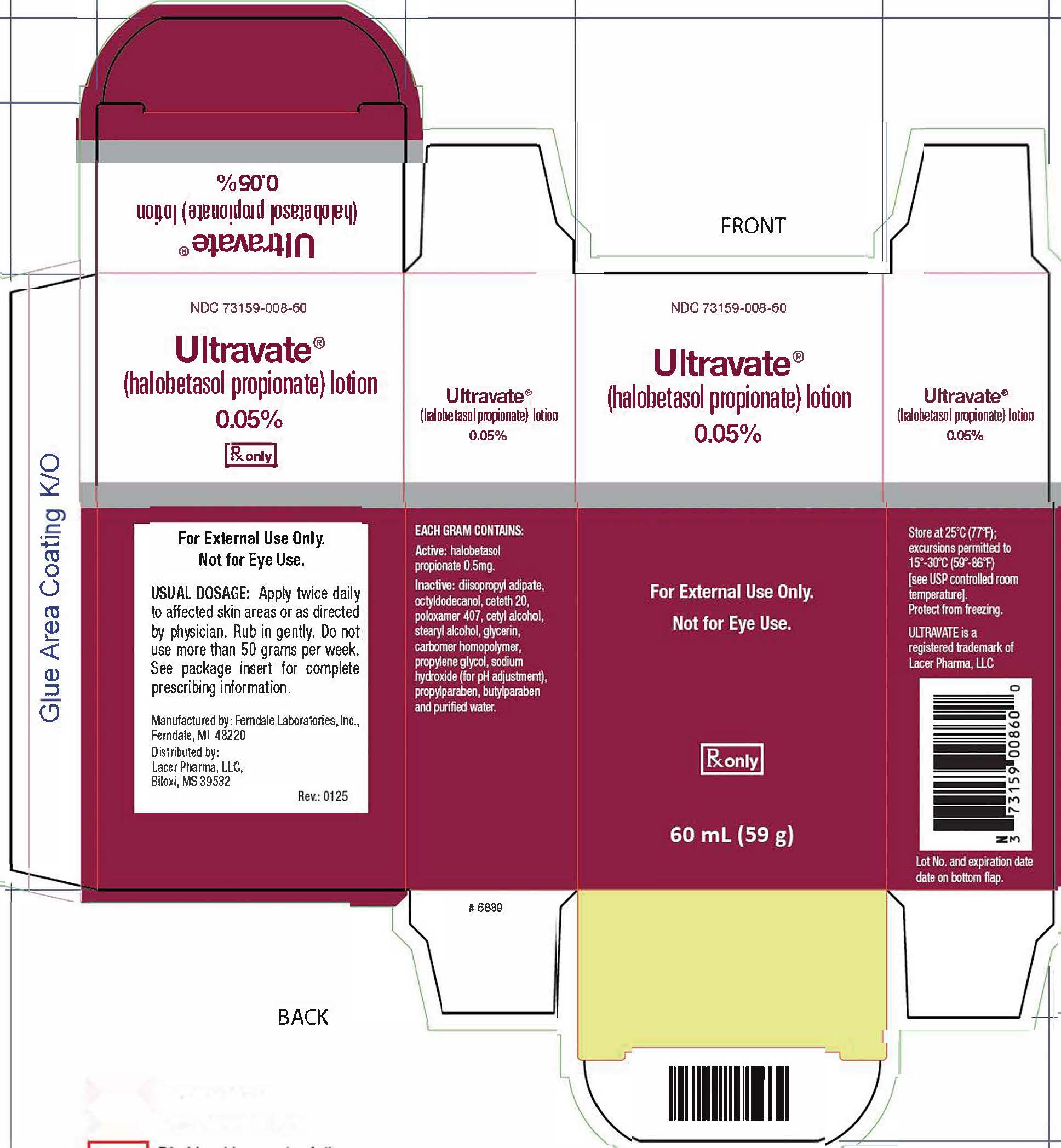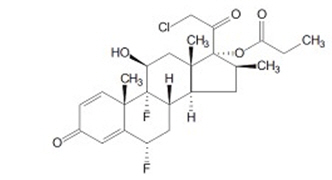 DRUG LABEL: ULTRAVATE
NDC: 73159-008 | Form: LOTION
Manufacturer: Lacer Pharma, LLC
Category: prescription | Type: HUMAN PRESCRIPTION DRUG LABEL
Date: 20250406

ACTIVE INGREDIENTS: HALOBETASOL PROPIONATE 0.5 mg/1 g
INACTIVE INGREDIENTS: DIISOPROPYL ADIPATE; OCTYLDODECANOL; CETETH-20; POLOXAMER 407; CETYL ALCOHOL; STEARYL ALCOHOL; PROPYLPARABEN; BUTYLPARABEN; PROPYLENE GLYCOL; GLYCERIN; CARBOMER HOMOPOLYMER, UNSPECIFIED TYPE; SODIUM HYDROXIDE; WATER

HIGHLIGHTS OF PRESCRIBING INFORMATION

These highlights do not include all the information needed to use ULTRAVATE® Lotion safely and effectively.
See full prescribing information for ULTRAVATE Lotion.
ULTRAVATE (halobetasol propionate) lotion, for topical use
Initial U.S. Approval: 1990

RECENT MAJOR CHANGES

Indication and Usage (1) | 08/2020
Warnings and Precautions (5.1) | 08/2020

1 INDICATIONS AND USAGE

ULTRAVATE lotion is a corticosteroid indicated for the topical treatment of plaque psoriasis in patients 12 years of age and older. (1)

2 DOSAGE AND ADMINISTRATION

- Apply a thin layer to the affected areas twice daily. (2)
- Limit use to 50 g/week. (2)
- Discontinue treatment when control is achieved. (2)
- If no improvement is seen within 2 weeks, reassess diagnosis. (2)
- Treatment beyond 2 consecutive weeks is not recommended. (2)
- Do not use with occlusive dressings unless directed by a physician. (2)
- Avoid use on the face, scalp, groin, or axillae. (2)
- Not for ophthalmic, oral, or intravaginal use. (2)

3 DOSAGE FORMS AND STRENGTHS

Lotion: 0.05% (0.5 mg/g). (3)

4 CONTRAINDICATIONS

None.

5 WARNINGS AND PRECAUTIONS

- Reversible hypothalamic-pituitary-adrenal (HPA) axis suppression may occur, with the potential for glucocorticosteroid insufficiency during or after treatment. Systemic absorption may require evaluation for HPA axis suppression. (5.1)
- Systemic effects of topical corticosteroids may also include Cushing's syndrome, hyperglycemia, and glucosuria. Use of potent corticosteroids on large areas, for prolonged durations, under occlusive dressings, or on an altered skin barrier may increase systemic exposure. (5.1)
- Children may be more susceptible to systemic toxicity when treated with topical corticosteroids. (5.1, 8.4)
- Local adverse reactions with topical steroids may include atrophy, striae, irritation, acneiform eruptions, hypopigmentation, and allergic contact dermatitis. Adverse reactions may be more likely to occur with occlusive use or more potent corticosteroids. (5.2, 5.5)
- Topical corticosteroids may increase the risk of cataract and glaucoma formation. If visual symptoms occur, consider referral to an ophthalmologist tor evaluation. (5.3)
- Initiate appropriate therapy if concomitant skin infections develop. (5.4)

6 ADVERSE REACTIONS

The most commonly reported adverse reactions (≥1%) are telangiectasia, application site atrophy, and headache. (6.1)

To report SUSPECTED ADVERSE REACTIONS, contact LAcer Pharma, LLC at 1-888-403-8874 or FDA at 1-800-FDA-1088 or www.fda.gov/medwatch.

FULL PRESCRIBING INFORMATION

1 INDICATIONS AND USAGE

ULTRAVATE lotion is indicated for the topical treatment of plaque psoriasis in patients 12 years of age and older.

2 DOSAGE AND ADMINISTRATION

Apply a thin layer of ULTRAVATE lotion to the affected skin twice daily for up to two weeks. Rub in gently.

Discontinue therapy when control is achieved. If no improvement is seen within two weeks, reassessment of diagnosis may
be necessary.

Treatment beyond two weeks is not recommended and the total dosage should not exceed 50 grams (50 ml) per week because of the potential for the drug to suppress the hypothalamic-pituitary-adrenal (HPA) axis {see Warnings and Precautions 5.1].Do not use with occlusive dressings unless directed by a physician.

ULTRAVATE lotion is for external use only.

Avoid use on the face, scalp, groin, or axillae.

ULTRAVATE lotion is not for ophthalmic, oral, or intravaginal use.

3 DOSAGE FORMS AND STRENGTHS

ULTRAVATE (halobetasol propionate) lotion, 0.05% is a white to off-white lotion. Each gram of ULTRAVATE lotion contains 0.5 mg of halobetasol propionate.

4 CONTRAINDICATIONS

None.

5 WARNINGS AND PRECAUTIONS

5.1 Effects on Endocrine System

ULTRAVATE lotion has been shown to suppress the hypothalamic-pituitary-adrenal (HPA) axis.Systemic effects of topical corticosteroids may include reversible HPA axis suppression, with the potential for glucocorticosteroid insufficiency. This may occur during treatment or upon withdrawal of treatment of the topical corticosteroid.The potential for hypothalamic-pituitary adrenal (HPA) suppression with ULTRAVATE lotion was evaluated in the following studies:

- In a study of 20 adult subjects with moderate to severe plaque psoriasis involving 􀃙20% of their body surtace area. ULTRAVATE lotion produced HPA axis suppression when used twice daily for two weeks in 5 out of 20 (25%) adult subjects with plaque psoriasis. The effects of HPA axis suppression were reversible on discontinuation of the treatment [see Clinical Pharmacology (12.2)].
- In another clinical study, 16 adolescent subjects (12 to less than 17 years old) with moderate to severe plaque psoriasis involving 10% or more of their body surtace area applied a maximum of approximately 50 grams of ULTRAVATE lotion to affected areas twice daily for two weeks. Of the 14 subjects evaluated for HPA axis suppression, adrenal suppression occurred in 1 subject (7%) which recovered upon retest [see Clinical Pharmacology (12.2)].

Because of the potential for systemic absorption, use of topical corticosteroids, including ULTRAVATE lotion, may require that patients be evaluated periodically for evidence of HPA axis suppression. Factors that predispose a patient using a topical corticosteroid to HPA axis suppression include the use of more potent corticosteroids, use over large surtace areas, prolonged use, occlusive use, use on an altered skin barrier, concomitant use of multiple corticosteroid-containing products, liver failure, and young age. An ACTH stimulation test may be helpful in evaluating patients for HPA axis suppression.If HPA axis suppression is documented, attempt to gradually withdraw the drug, reduce the frequency of application, or substitute a less potent steroid. Manifestations of adrenal insufficiency may require supplemental systemic corticosteroids. Recovery of HPA axis function is generally prompt and complete upon discontinuation of topical corticosteroids.Systemic effects of topical corticosteroids may also include Cushing's syndrome, hyperglycemia, and glucosuria. Use of more than one corticosteroid-containing product at the same time may increase the total systemic exposure to topical corticosteroids. Pediatric patients may be more susceptible than adults to systemic toxicity from the use of topical corticosteroids due to their larger surtace-to-body mass ratios [see Use in Specific Populations (8.4)].

5.2 Local Adverse Reactions

Local adverse reactions from topical corticosteroids may include atrophy, striae, telangiectasias, burning, itching, irritation, dryness, folliculitis, acneiform eruptions, hypopigmentation, perioral dermatitis, allergic contact dermatitis, secondary infection, and miliaria. These may be more likely to occur with occlusive use, prolonged use, or use of higher potency corticosteroids, including ULTRAVATE lotion. Some local adverse reactions may be irreversible.

5.3 Ophthalmic Adverse Reactions

Use of topical corticosteroids may increase the risk of posterior subcapsular cataracts and glaucoma. Cataracts and glaucoma have been reported in postmarketing experience with the use of topical corticosteroid products.

Advise patients to report any visual symptoms and consider referral to an ophthalmologist for evaluation.

5.4 Concomitant Skin Infections

Use an appropriate antimicrobial agent if a skin infection is present or develops. If a favorable response does not occur promptly, discontinue use of ULTRAVATE lotion until the infection has been adequately treated.

5.5 Allergic Contact Dermatitis

Allergic contact dermatitis with corticosteroids is usually diagnosed by observing failure to heal rather than noting a clinical exacerbation. Consider confirmation of a clinical diagnosis of allergic contact dermatitis by appropriate patch testing. Discontinue ULTRAVATE lotion if allergic contact dermatitis is established.

6 ADVERSE REACTIONS

6.1 Clinical Trials Experience

Because clinical trials are conducted under widely varying conditions, adverse reaction rates observed in the clinical trials of a drug cannot be directly compared to rates in the clinical trials of another drug and may not reflect the rates observed in practice.

During randomized, controlled, blinded clinical trials 277 adults with plaque psoriasis were treated with ULTRAVATE lotion twice daily for up to two weeks (up to approximately 50 grams/week).

Table 1 presents adverse reactions that occured in at least 1% of subjects treated with ULTRAVATE lotion twice daily for up to two weeks, and more frequently than in vehicle-treated subjects.

Table 1: Adverse Reactions Occurring in ≥ 1% of Subjects Treated with ULTRAVATE Lotion for up to Two Weeks
 | ULTRAVATE Lotion (N=277) | Vehicle Lotion (N=259)
Adverse Reaction | % | %
Telangiectasia | 1% | 0%
Application site atrophy | 1% | <1%
Headache | 1% | <1%

Less common dverse reactions (incidence less than 1% but greater than 0.1%) that occured in subjects treated with ULTRAVATE lotion included application site discoloration, herpes zoster, influenza, nasopharyngitis, otitis media acute, throat infection, wound, and increased blood pressure.

8 USE IN SPECIFIC POPULATIONS

8.1 Pregnancy

There are no available data on Ultravate lotion use in pregnant women to inform a drug-associated risk of major birth defects, miscarriage, or adverse maternal or fetal outcomes. Published data report an increased risk of low birthweight with the use of greater than 300 grams of potent or very potent topical corticosteroid during pregnancy. In animal reproduction studies, halobetasol propionate administered systemically during organogenesis to pregnant rats at 13 and 33 times the human topical dose and to pregnant rabbits at 3 times the human topical dose resulted in teratogenic and embryotoxic effects [see Data]. The clinical relevance of the animal findings is not clear.

The background risk of major birth defects and miscarriage for the indicated population are unknown. In the U.S. general population, the estimated background risk of major birth defects and miscarriage in clinically recognized pregnancies is 2-4% and 15-20%, respectively.

Data

Human Data
Multiple observational studies found no significant associations between maternal use of topical corticosteroids of any potency and congenital malformations, preterm delivery, or fetal mortality. However, when the dispensed amount of potent or very potent topical corticosteroid exceeded 300 g during the entire pregnancy, use was associated with an increase in low birth weight infants.

Animal Data

Halobetasol propionate has been shown to be teratogenic in rats and rabbits when given systemically during organogenesis at doses of 0.04 to 0.1 mg/kg/day in rats and 0.01 mg/kg/day in rabbits. These doses are approximately 13, 33, and 3 times, respectively, the human topical dose of halobetasol propionate, 0.05%. Halobetasol propionate was embryotoxic in rabbits but not in rats.Cleft palate was observed in both rats and rabbits. Omphalocele was seen in rats, but not in rabbits.

8.2 Lactation

Risk Summary

There are no data on the presence of halobetasol propionate or its metabolites in human milk, the effects on the breastted infant, or the effects on milk production after topical application to women who are breastteeding.

Systemically administered corticosteroids appear in human milk and could suppress growth, intertere with endogenous corticosteroid production, or cause other untoward effects. It is not known whether topical administration of corticosteroids could result in sufficient systemic absorption to produce detectable quantities in human milk. The developmental and health benefits of breastteeding should be considered along with the mother's clinical need for UL TRAVATE lotion and any potentialadverse effects on the breastted infant from ULTRAVATE lotion or from the underlying maternal condition.

Clinical Considerations

Advise breastfeeding women not to apply ULTRAVATE lotion directly to the nipple and areola to avoid direct infant exposure.

8.4 Pediatric Use

Safety and effectiveness of ULTRAVATE lotion for the treatment of moderate to severe plaque psoriasis have been established in patients 12 years of age and older. It is supported by evidence from adequate and well-controlled trials in adults and from one uncontrolled safety trial in 16 adolescents (12 to less than 17 years of age). Adolescent patients with moderate to severe plaque psoriasis covering a minimum of 10% of the total body surface area were treated twice daily for 2 weeks with ULTRAVATE lotion. Hypothalamic-pituitary adrenal (HPA) axis function (ACTH stimulation test) was evaluated in a subset of 14 patients. After 2 weeks of treatment, 1 of 14 patients (7%) experienced laboratory evidence of adrenal suppression (i.e., cortisol serum level of sl 8 μg/dL) that recovered upon retest. No other adverse reactions were reported in the study.

Because of higher skin surtace area to body mass ratios, pediatric patients are at a greater risk than adults of HPA axis suppression and Cushing's syndrome when they are treated with topical corticosteroids. They are therefore also at greater risk of adrenal insufficiency during or after withdrawal of treatment. Adverse reactions including striae have been reported with use of topical corticosteroids in infants and children.

HPA axis suppression, Cushing's syndrome, linear growth retardation, delayed weight gain, and intracranial hypertension have been reported in children receiving topical corticosteroids. Manifestations of adrenal suppression in children include low plasma cortisol levels and an absence of response to ACTH stimulation. Manifestations of intracranial hypertension include bulging fontanelles, headaches, and bilateral papilledema.

8.5 Geriatric Use

Clinical studies with ULTRAVATE lotion included 89 subjects aged 65 years and over. No overall differences in safety or effectiveness were observed between these subjects and those younger than 65 years. Clinical studies of ULTRAVATE lotion did not include sufficient numbers of subjects aged 65 and over to determine whether they respond differently from younger subjects.

10 OVERDOSAGE

Topically applied ULTRAVATE lotion can be absorbed in sufficient amounts to produce systemic effects [see Warnings and Precautions (5.1)].

11 DESCRIPTION

ULTRAVATE (halobetasol propionate) lotion, 0.05% for topical use contains a corticosteroid, halobetasol propionate. The chemical name of halobetasol propionate is 21 chloro-6α, 9-difluoro-11β, 17-dihydroxy-16β-methylpregna-1, 4-diene-3,20-dione 17 propionate. Halobetasol propionate is a white to off-white crystalline powder with a molecular weight of 484.96 and a molecular formula of C25H31ClF2O5. It is practically insoluble in water and freely soluble in dichloromethane and in acetone. It has the following structural formula:

Each gram of ULTRAVATE lotion contains 0.5 mg of halobetasol propionate in a white to off-white lotion base consisting of diisopropyl adipate, octyldodecanol, ceteth-20, poloxamer 407, cetyl alcohol, stearyl alcohol, propylparaben, butylparaben, propylene glycol, glycerin, carbomer homopolymer, sodium hydroxide, and water.

12 CLINICAL PHARMACOLOGY

12.1 Mechanism of Action

Corticosteroids play a role in cellular signaling, immune function, inflammation, and protein regulation; however, the precise mechanism of action in plaque psoriasis is unknown.

12.2 Pharmacodynamics

Vasoconstriction:
A vasoconstrictor assay in healthy subjects with ULTRAVATE lotion indicated that the formulation is in the super-high range of potency as compared to other topical corticosteroids; however, similar blanching scores do not necessarily imply therapeutic equivalence.

Hypothalamic-Pituitaty-Adrenal (HPA) Axis Suppression:

The potential for hypothalamic-pituitary adrenal (HPA) suppression was evaluated in the following two studies. In both studies, the criteria for HPA-axis suppression was a serum cortisol level of less than or equal to 18 micrograms per deciliter 30 minutes after stimulation with cosyntropin (adrenocorticotropic hormone, ACTH). In the first study, ULTRAVATE lotion was applied to20 adult subjects with moderate to severe plaque psoriasis. A mean dose of 3.5 grams ULTRAVATE lotion was applied twice daily for two weeks and produced HPA axis suppression in 5 of 20 (25%) subjects. The effects of HPA axis suppression were reversible on retesting at least four weeks after discontinuation of the treatment. In the second study, ULTRAVATE lotion was applied to 16 adolescent subjects 12 years to less than 17 years of age with moderate to severe plaque psoriasis affecting a mean body surtace area of 11.5% (range from 10% to 14%). The mean dose was 3.6 grams applied twice daily for two weeks. A subset of 14 of the 16 completed subjects had evaluable ACTH stimulation tests, and HPA axis suppression was observed in 1 of these 14 subjects (7%). In the second study also, the effects of HPA axis suppression were reversible on retesting at least four weeks after discontinuation of the treatment.

12.3 Pharmacokinetics

The extent of percutaneous absorption of topical corticosteroids is determined by many factors, including the vehicle, the integrity of the epidermal barrier, and the use of occlusive dressings. Topical corticosteroids can be absorbed from normal intact skin. Inflammation and/or other disease processes in the skin may increase percutaneous absorption.

In the HPA clinical study /see Clinical Pharmacology (12.2)1, pharmacokinetics was evaluated in a subgroup of 12 adult subjects. On Day 8, blood was taken just prior to and at 1, 2, 4, 6, 8, and 12 hours following the last application. Plasma concentration of halobetasol propionate (HBP) was measurable in all subjects. Based on the geometric mean plasma concentrations at 12 hours post-application across time, steady-state was achieved by Day 8. The mean (±standard deviation) Cmaxconcentrations for ULTRAVATE lotion on Day 8 was 201.1 ± 157.5 pg/ml, with the corresponding median Tmaxvalue of 3 hours (range O - 6 hours); mean area under the halobetasol propionate concentration versus time curve over the dosing interval (AUCt) was 1632 ± 1147 pg•h/ml.

Specific Populations
Pediatric Patients

In the pediatric HPA study [see Clinical Pharmacology (12.2)], trough plasma concentrations of HBP were measured on Day 8 and Day 15 in a subset of 14 subjects. The HBP levels in the plasma were below the quantification limit (20 pg/ml) for all subjects at all time points with the exception of one subject at Day 15 (trough concentration of HBP of 28.2 pg/ml).

13 NONCLINICAL TOXICOLOGY

13.1 Carcinogenesis, Mutagenesis, Impairment of Fertility

Long-term animal studies have not been performed to evaluate the carcinogenic potential of halobetasol propionate.

In a 90-day repeat-dose toxicity study in rats, topical administration of Halobetasol Propionate Topical Foam at dose concentrations from 0.005% to 0.05% or from 0.011 to 0.11 mg/kg/day of halobetasol propionate resulted in a toxicity profile consistent with long-term exposure to corticosteroids including adrenal atrophy, histopathological changes in several organ systems indicative of severe immune suppression, and opportunistic fungal and bacterial infections. A no observable adverse effect level could not be determined in this study. Although the clinical relevance of the findings in animals to humans is not clear, sustained glucocorticoid-related immune suppression may increase the risk of infection and possibly the risk of carcinogenesis.

Halobetasol propionate was not found to be genotoxic in the Ames/Salmonella assay, in the Chinese hamster CHO/HGPRT assay, in the mouse micronucleus test, in the sister chromatid exchange test in somatic cells of the Chinese hamster, or in the chromosome aberration test in somatic cells of Chinese hamsters. Positive mutagenicity effects were observed in two genotoxicity assays: Chinese hamster nuclear anomaly test and mouse lymphoma gene mutation assay in vitro.

Studies in the rat following oral administration at dose levels up to 0.05 mg/kg/day indicated no impairment of fertility or general reproductive performance.

14 CLINICAL STUDIES

ULTRAVATE lotion was evaluated for the treatment of moderate to severe plaque psoriasis in two multicenter, randomized, doble-blind, vehicle-controlled trials.

These trials were conducted in 443 subjects 18 years of age and older with plaque psoriasis involving between 2% and 12% body surface area. Baseline disease severity was determined using a static, five-level global evaluation scale, on which a subject scored either moderate or severe. Overall, 57% of subjects were male and 86% were Caucasian.

Subjects applied ULTRAVATE lotion or vehicle to all affected areas twice daily for up to 14 consecutive days.

The primary measure of efficacy was Overall Treatment Success, defined as the proportion of subjects who were cleared or almost cleared with at least a two grade improvement from baseline at Week 2 (end of treatment). Table 2 presents these results.

Table 2: Overall Treatment Success in Subjects with Plaque Psoriasis at Week 2
 | Study 1 |  | Study 2
 | ULTRAVATE Lotion N=110 | Vehicle Lotion N=76 | ULTRAVATE Lotion N=110 | Vehicle Lotion N=112
Overall Treatment Success [Subject whose condition was cleared or almost cleared of all signs of psoriasis and with at least a two grade improvement from baseline.] | 49 (44.5%) | 7 (6.3%) | 49 (44.5%) | 8 (7.1%)

The secondary measures of efficacy were Treatment Success for individual signs of psoriasis (scaling, erythema, and plaque
elevation) at the end of treatment (see Table 3).

Table 3: Individual Signs Treatment Success in Subjects with Plaque Psoriasis at Week 2
 | Study 1 |  | Study 2
Treatment Success [Subjects who were cleared or almost cleared of the designated clinical sign with at least a two grade improvement from baseline.] | ULTRAVATE Lotion N=10 | Vehicle Lotion N=111 | ULTRAVATE Lotion N=110 | Vehicle Lotio N=112
Scaling | 61 (55.5%) | 12 (10.8%) | 65 (59.1%) | 11 (9.8%)
Erythema | 40 (36.4%) | 8 (7.2%) | 48 (43.6%) | 12 (10.7%)
Plaque Elevation | 50 (45.5%) | 9 (8.1%) | 48 (43.6%) | 9 (8.0%)

16 HOW SUPPLIED/STORAGE AND HANDLING

ULTRAVATE lotion, 0.05 % is white to off-white lotion. It is supplied in an oval tapered white high-density polyethylene bottle with a white polypropylene disc cap. Each bottle contains 60 ml (59 g) of ULTRAVATE lotion.

NOC 73159-008-60 60 ml (59 g) bottle

Store at 25'C (77'F); excursions permitted to 15°G and 30°G (59° F to 86°F) [see USP Controlled Room Temperature]. Do not freeze.

17 PATIENT COUNSELING INFORMATION

Advise the patient to read the FDA-approved patient labeling (Patient Information).

Advise patients using ULTRAVATE lotion of the following information and instructions:

Important Administration Instructions

Instruct patients to discontinue ULTRAVATE lotion when psoriasis is controlled. ULTRAVATE lotion should not be used for longer than 2 weeks. Advise patients to contact the physician if no improvement is seen within 2 weeks. Inform patients that total dosage should not exceed 50 grams per week [see Dosage and Administration (2)].

Instruct patients to avoid bandaging, wrapping or otherwise occluding the treatment area(s), unless directed by physician. Advise patients to avoid use on the face, scalp, groin, or axillae [see Dosage and Administration (2)].

Effects on Endocrine System

UL TRAVATE lotion may cause HPA axis suppression. Advise patients that use of UL TRAVATE lotion, may require periodic evaluation for HPA axis suppression. Advise patients to avoid use of multiple corticosteroid-containing products [see Warnings and Precautions (5.1)].

Local Adverse Reactions

Inform patients that topical corticosteroids may cause local adverse reactions, some of which may be irreversible. These reactions may be more likely to occur with occlusive use, prolonged use or use of higher potency comcosteroids, including ULTRAVATE lotion [see Warnings and Precautions (5.2)].

Breastteeding women should not apply ULTRAVATE lotion directly to the nipple and areola to avoid directly exposing the infant [see Lactation (8.2)].

ULTRAVATE is a trademark of Lacer Pharma, LLC
Manufactured by: Ferndale Laboratories, Inc., Ferndale, Ml 48220
Distributed by: Lacer Pharma, LLC, Biloxi, MS 39532
U.S. Patent 8,962,028
Document Control No. 69311.
Rev.: 0125

PRINCIPAL DISPLAY PANEL - 50 g Canister Carton

NDC 73159-008-60

ULTRAVATE lotion, 0.05%

For topical use only.

Rx ONLY

Net Wt. 60 mL (59 g) bottle